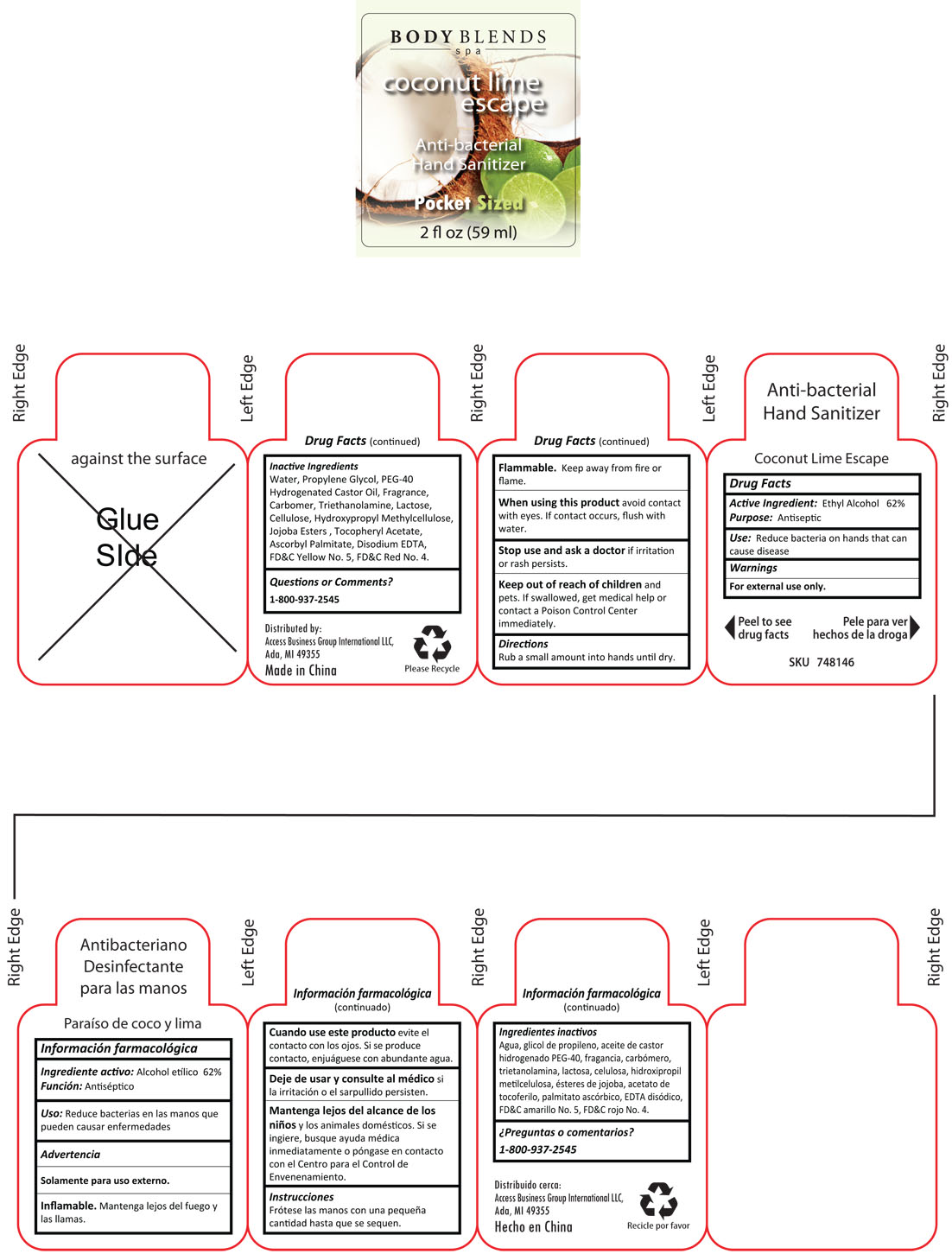 DRUG LABEL: Body Blends Coconut Lime Escape Anti-bacterial Hand Sanitizer
NDC: 49981-020 | Form: LIQUID
Manufacturer: Xiamen Anna Global Co., Ltd
Category: otc | Type: HUMAN OTC DRUG LABEL
Date: 20100705

ACTIVE INGREDIENTS: ALCOHOL 62.00 g/100 g
INACTIVE INGREDIENTS: WATER 34.04959 g/100 g; PROPYLENE GLYCOL 1.8 g/100 g; POLYOXYL 40 HYDROGENATED CASTOR OIL 1.0 g/100 g; CARBOMER COPOLYMER TYPE A 0.29 g/100 g; TROLAMINE 0.28 g/100 g; ANHYDROUS LACTOSE 0.01 g/100 g; CELLULOSE, MICROCRYSTALLINE 0.01 g/100 g; EDETATE DISODIUM 0.03 g/100 g; FD&C RED NO. 4 0.00004 g/100 g; FD&C YELLOW NO. 5 0.00037 g/100 g; HYPROMELLOSE 2208 (15000 CPS) 0.01 g/100 g; ALPHA-TOCOPHEROL ACETATE 0.01 g/100 g; ASCORBYL PALMITATE 0.01 g/100 g; COCONUT 0.25 g/100 g; LIME 0.25 g/100 g

Drug Fact

Active ingredients Purpose

Ethyl Alcohol 62% Antiseptic

DESCRIPTION

Uses Reduce bacteria on hands that can cause disease

Warnings

For external use only

Flammable: Keep away from fire or flame

When using this product，avoid contact with eyes. If contact occurs, flush with water

Stop using and ask a doctor, if irritation or rash persists

Keep out of reach of children and pets. If swallowed, get medical help or contact a Poison Control Center immediately.

Directions

Rub a small amount into hands until dry

Inactive ingredients

Water, Propylene Glycol, PEG-40 Hydrogenated Castor Oil, Fragrance, Carbomer, Triethanolamine, Lactose, Cellulose, Hydroxypropyl Methylcellulose, Jojoba Ester, Tocopheryl Acetate, Ascorbyl Palmitate, Disodium EDTA, FD and C red No. 4, FD and C Yellow No. 5

PACKAGE LABEL

lab